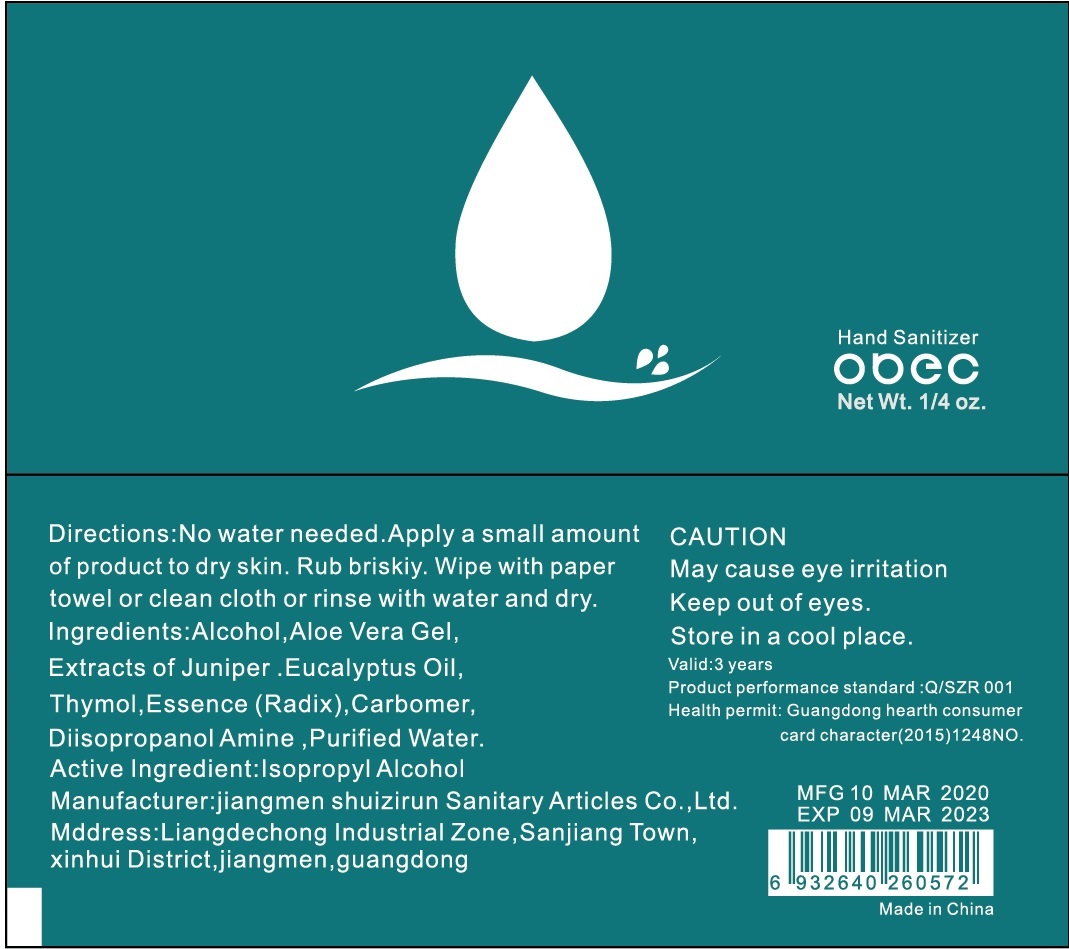 DRUG LABEL: OBEC hand sanitizer
NDC: 71734-316 | Form: LIQUID
Manufacturer: JIANGMEN SHUIZIRUN SANITARY ARTICLES CO., LTD.
Category: otc | Type: HUMAN OTC DRUG LABEL
Date: 20200622

ACTIVE INGREDIENTS: ALCOHOL 62 mL/100 mL
INACTIVE INGREDIENTS: GLYCERIN; CARBOMER 934; WATER; TROLAMINE; EDETATE DISODIUM

Drug Fact

Active Ingredient

Ethyl Alcohol 62%

Purpose

Antiseptic

Uses

- decrease bacteria and germs on the hands
- use when soap , towel and water are not available.
- recommended for repeared use.

Warnings

For external use only.

Stop use and ask a doctor ifirritation or redness develops or persists.

Flammable, keep away from fire or flame

Do not apply around eyes.

Do not use in ears and mouth

Other information:

- store at 20℃ (68 to 77 ℉)
- may discolor fabrics

WHEN USING

avoid contact with eyes. In case of contact flush eyes with water

consult a physicia

if irritation or redness develops or persists

Keep out of reach of children.

Children under 6, use only under adult supervision. Not recommended for infants.

Directions

No water needed. Apply a small amount of product to dry skin. Rub briskly. wipe with paper towel or clean cloth or rinse with water and dry.

Inactive Ingredients

Aloe vera Gel, Extracts of juniper, Eucalyptus oil, Thymol, Essence (Radlx), Carbomer, Diisopropanol amine, Purified water